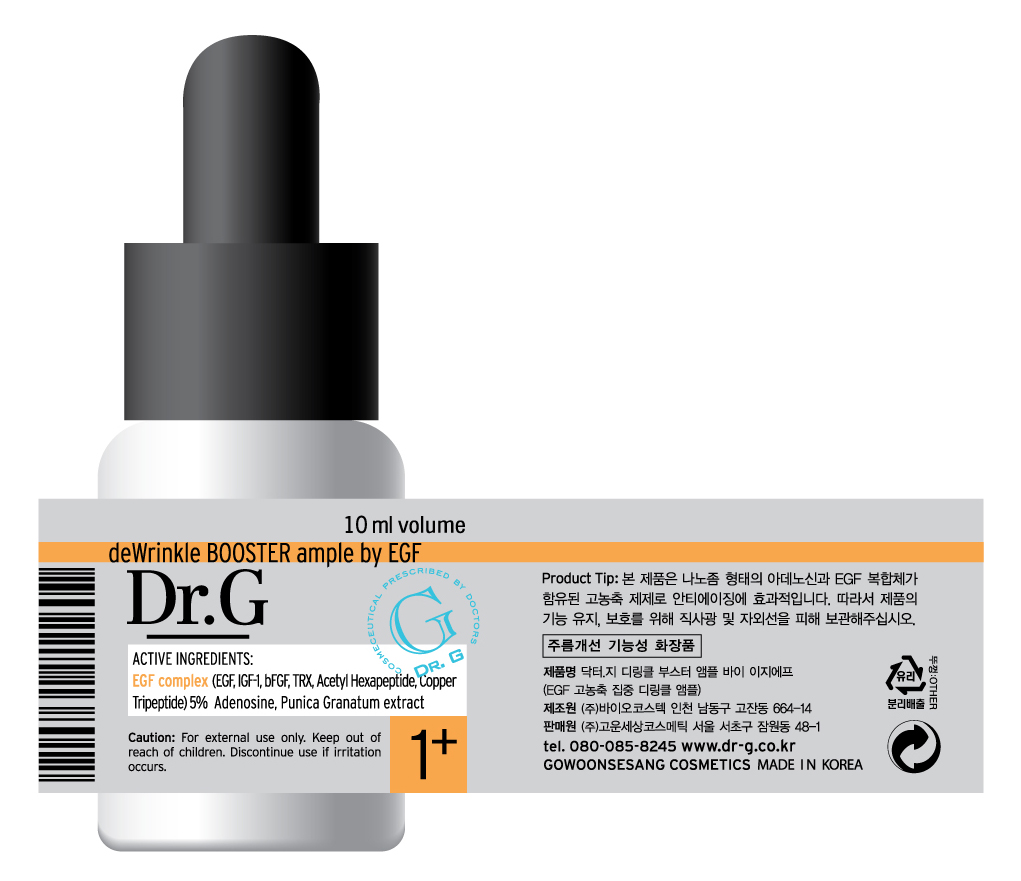 DRUG LABEL: Dr G deWrinkle BOOSTER ample by EGF
NDC: 43948-3001 | Form: SOLUTION/ DROPS
Manufacturer: The Doctor's Cosmetic Inc
Category: otc | Type: HUMAN OTC DRUG LABEL
Date: 20091001

ACTIVE INGREDIENTS: ADENOSINE 0.04 mL/10 mL; GLYCERIN 0.5 mL/10 mL

WHEN USING

DIRECTION OF USE:

After conditioning skin with Regulator(toner) take 2 to 3 droplets and spread over the entire face. Place both hands over the face to allow deep absorption with warmth of hands. Apply AM and PM to feel the refreshing skin. Keep away from children.

KEEP OUT OF REACH OF CHILDREN

Caution: For external use only. Keep out of reach of children. Discontinue use if irritation occurs.

ACTIVE INGREDIENTS:

Glycerin, EGF Complex (EGF, IGF-1, bFGF, TRX, Acetyl Hexapeptide, Copper Tripeptide) 5% Adenosine, Punica Granatum extract

PACKAGE LABEL

Label5e